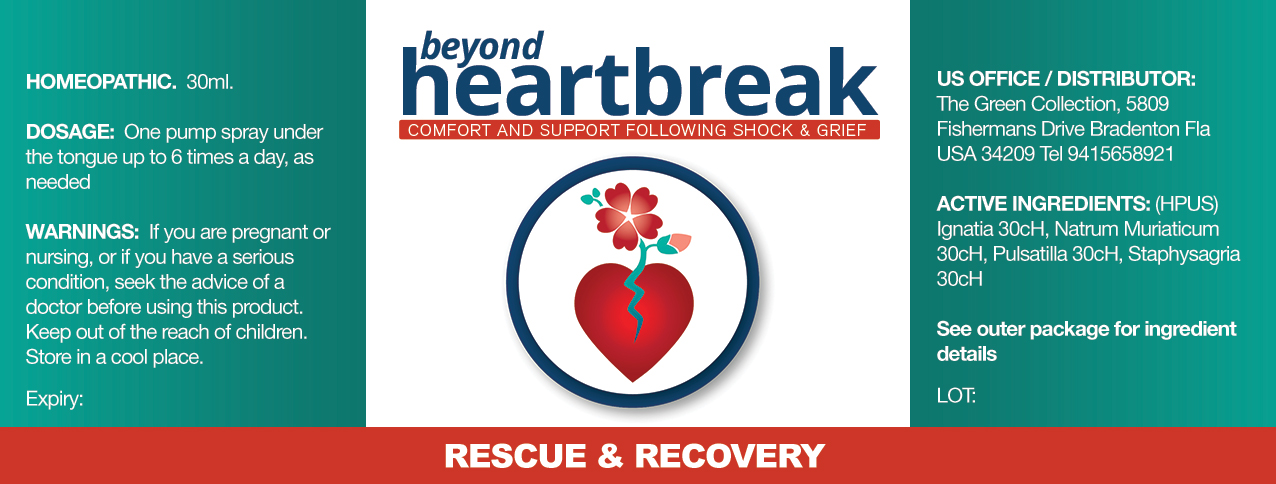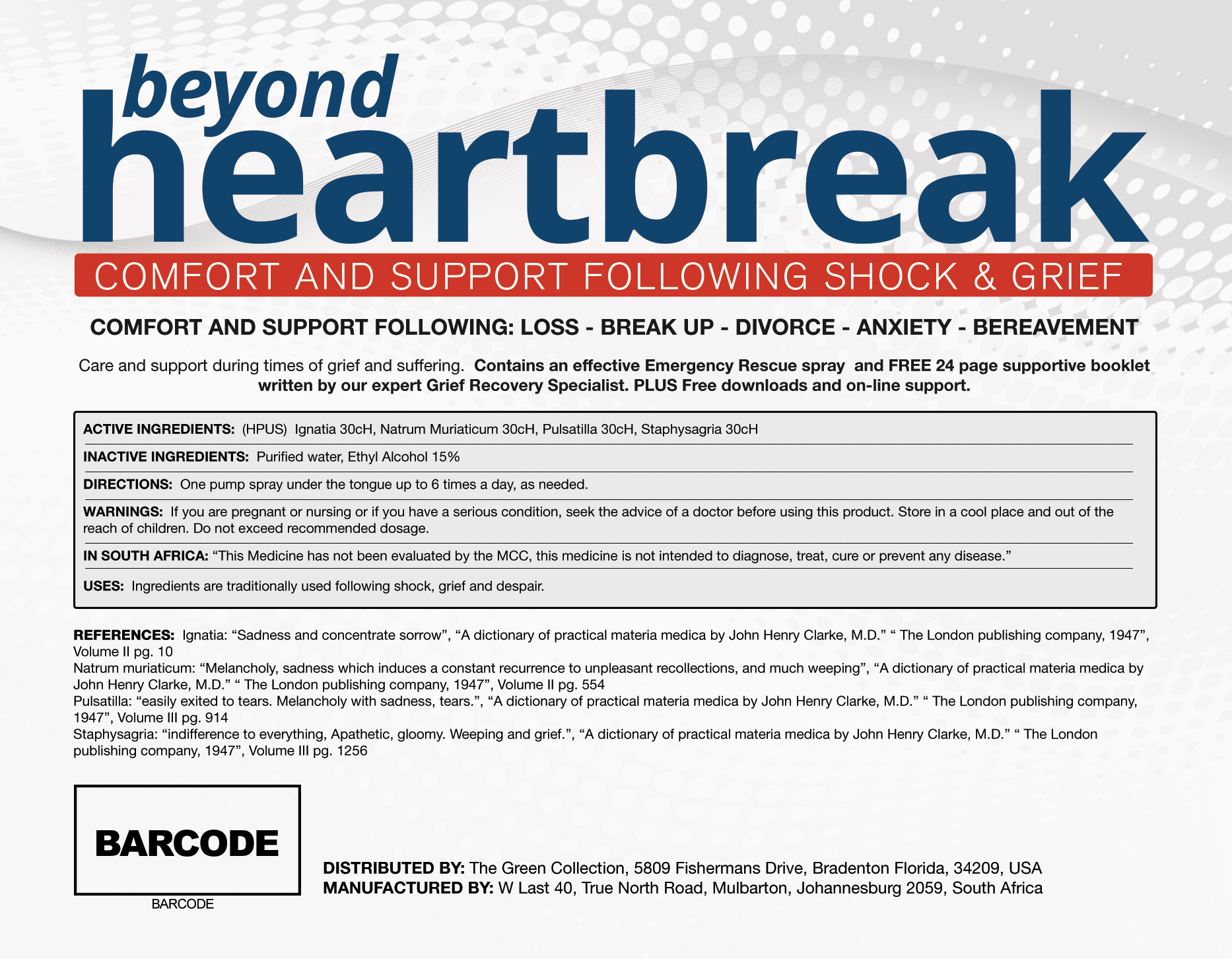 DRUG LABEL: beyond heartbreak
NDC: 58214-123 | Form: SPRAY
Manufacturer: JMSP USA LLC
Category: homeopathic | Type: HUMAN OTC DRUG LABEL
Date: 20170612

ACTIVE INGREDIENTS: STRYCHNOS IGNATII SEED 30 [hp_C]/30 mL; SODIUM CHLORIDE 30 1/30 mL; ANEMONE PULSATILLA 30 1/30 mL; DELPHINIUM STAPHISAGRIA SEED 30 1/30 mL
INACTIVE INGREDIENTS: WATER; ALCOHOL

Beyond heartbreak

Ingredients:

Ignatia (STRYCHNOS IGNATII SEED) 30 cH

NatrumMuriaticum (SODIUM CHLORIDE) 30 cH

Pulsatilla (ANEMONE PULSATILLA) 30 cH

Staphysagria (DELPHINIUM STAPHISAGRIA SEED) 30 cH

Purpose of ingredients:

Comfort and Support Following LOSS- BREAK UP DIVORCE ANXIETY BEREAVEMENT

Keep out of reach of children

Warnings:

- Not intended for pregnant or lactating women
- Not to be taken by those with existing medical conditions, please consult your physician prior to use.

Indications and Usage:

Comfort and Support Following LOSS- BREAK UP DIVORCE ANXIETY BEREAVEMENT

Inactive Ingredients:

Purified Water and Ethyl Alcohol

Directions

One pump spray under the tongue up to 6 times a day, or as needed